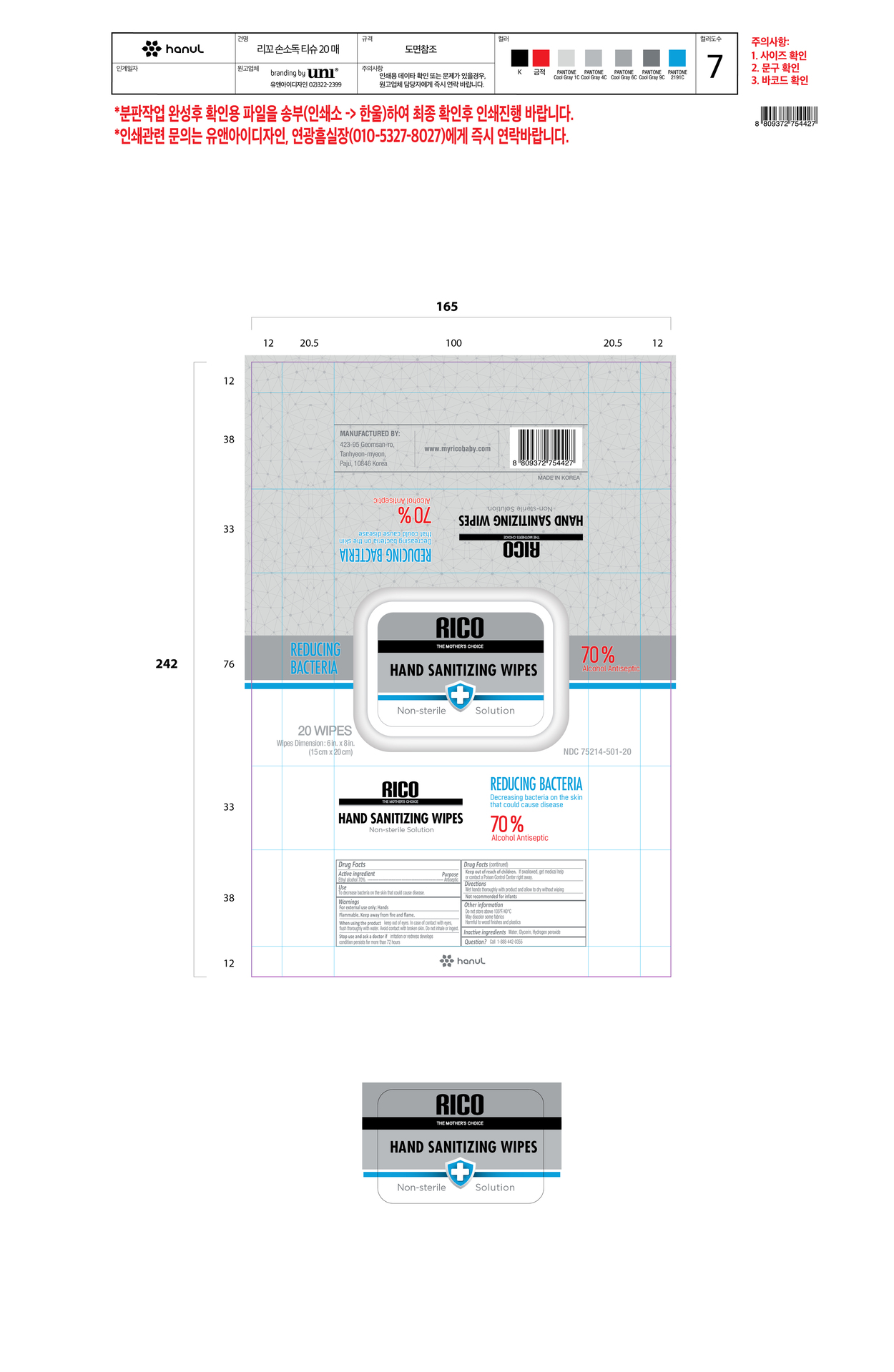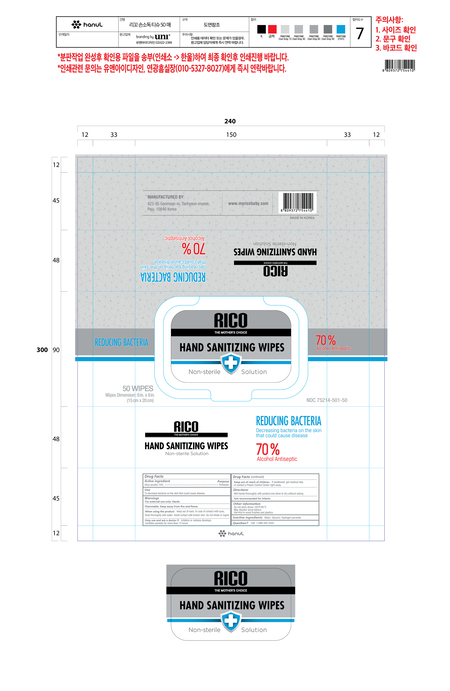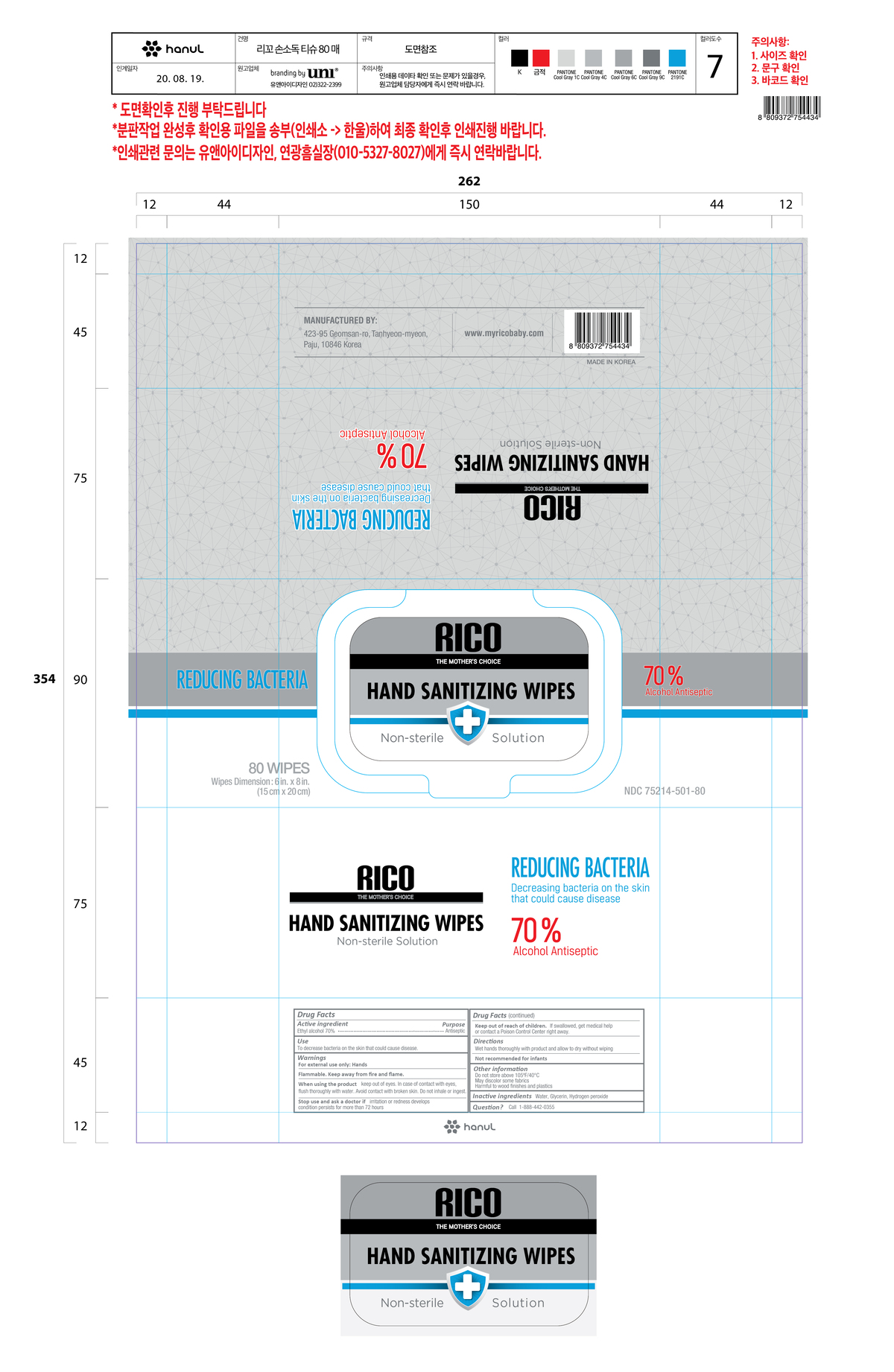 DRUG LABEL: Hand Sanitizer Wipes
NDC: 75214-501 | Form: CLOTH
Manufacturer: HANUL CO.,LTD
Category: otc | Type: HUMAN OTC DRUG LABEL
Date: 20250120

ACTIVE INGREDIENTS: ALCOHOL 70 mL/100 mL
INACTIVE INGREDIENTS: GLYCERIN 1.83 mL/100 mL; HYDROGEN PEROXIDE 0.002 mL/100 mL; WATER

Rico Hand Sanitizing Wipes 70%

Active Ingredient(s)

Ethyl Alcohol 70% Purpose: Antiseptic

Purpose

Antiseptic, Hand Sanitizer Wipes

Use

To decrease bacteria on the skin that could cause disease

Warnings

For external use only: hands

Flammable. Keep away from fire and flame.

When using this product

keep out of eyes. In case of contact with eyes, flush thoroughly with water.

avoid contact with broken skin

do not inhale or ingest

Stop Use and ask a doctor if

irritation or redness develops

condition persists for more than 72 hours

Keep out of reach of children. If swallowed, get medical help or contact a Poison Control Center right away.

Directions

- Wet hands thoroughly with product and allow to dry without wiping
- Not recommended for infants

Other information

do not store above 105ºF/40°C

may discolor some fabrics

harmful to wood finishes and plastics

Inactive ingredients

water, glycerin, hydrogen peroxide

Package Label - Principal Display Panel

NDC: 75214-501-50

RICO HAND SANITIZING WIPES

NON STERILE SOLUTION

70% ALCOHOL ANTISEPTIC

Decreasing bacteria on the skin that could cause disease

50 wipes

wipes dimension 6in. x 8 In (15cm x 20m)